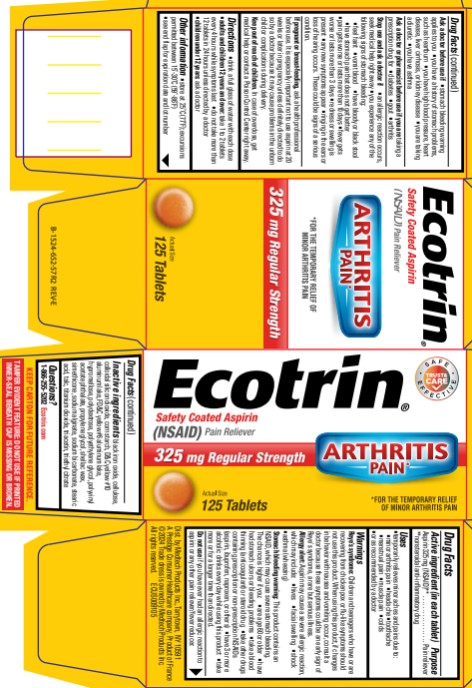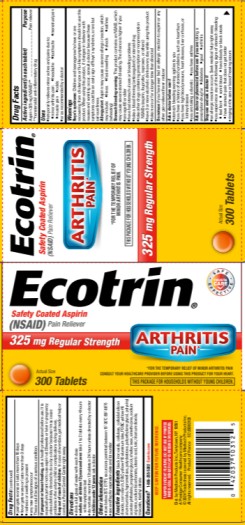 DRUG LABEL: Ecotrin Regular Strength
NDC: 63029-302 | Form: TABLET, COATED
Manufacturer: Medtech Products Inc.
Category: otc | Type: HUMAN OTC DRUG LABEL
Date: 20251023

ACTIVE INGREDIENTS: ASPIRIN 325 mg/1 1
INACTIVE INGREDIENTS: CARNAUBA WAX; SILICON DIOXIDE; EDETIC ACID; FD&C YELLOW NO. 6; GLYCERYL MONOSTEARATE; HYPROMELLOSES; METHYLPARABEN; METHACRYLIC ACID AND ETHYL ACRYLATE COPOLYMER; CELLULOSE, MICROCRYSTALLINE; POLYSORBATE 80; STARCH, CORN; PROPYLPARABEN; STEARIC ACID; TALC; TITANIUM DIOXIDE; TRIETHYL CITRATE

Ecotrin Regular

Drug Facts

Active ingredient

(in each tablet)

Aspirin (NSAID*) 325mg

*nonsteroidal anti-inflammatory drug

Purpose

Pain reliever

Uses

- temporarily relieves minor aches and pains due to:
  ▪ minor arthritis pain
  ▪ headache
  ▪ toothache
  ▪ menstrual pain
  ▪ muscle pain
  ▪ colds
- or as recommended by a doctor

Warnings

Reye’s syndrome: Children and teenagers who have or are recovering from chicken pox or flu-like symptoms should not use this product. When using this product, if changes in behavior with nausea and vomiting occur, consult a doctor because these symptoms could be an early sign of Reye’s syndrome, a rare but serious illness.

Allergy alert: Aspirin may cause a severe allergic reaction which may include:

- hives
- facial swelling
- shock
- asthma (wheezing)

Stomach bleeding warning: This product contains an NSAID, which may cause severe stomach bleeding. The chance is higher if you

- are age 60 or older
- have had stomach ulcers or bleeding problems
- take a blood thinning (anticoagulant) or steroid drug
- take other drugs containing prescription or nonprescription NSAIDs (aspirin, ibuprofen, naproxen, or others)
- have 3 or more alcoholic drinks every day while using this product
- take more or for a longer time than directed

Do not use

if you have ever had an allergic reaction to aspirin or any other pain reliever/fever reducer

Ask a doctor before use if

- stomach bleeding warning applies to you
- you have a history of stomach problems, such as heartburn
- you have high blood pressure, heart disease, liver cirrhosis, or kidney disease
- you are taking a diuretic
- you have asthma

Ask a doctor or pharmacist before use if you are

taking a prescription drug for

- diabetes
- gout
- arthritis

Stop use and ask a doctor if

- allergic reaction occurs,seek medical help right away.
- you experience any of the following signs of stomach bleeding:
  ▪ feel faint
  ▪ vomit blood
  ▪ have bloody or black stools
  ▪ have stomach pain that does not get better
- pain gets worse or lasts more than 10 days
- fever gets worse or lasts more than 3 days
- redness or swelling is present
- any new symptoms appear
- ringing in the ears or a loss of hearing occurs

These could be signs of a serious condition.

If pregnant or breast-feeding,

ask a health professional before use. It is especially important not to use aspirin at 20 weeks or later in pregnancy unless definitely directed to do so by a doctor because it may cause problems in the unborn child or complications during delivery.

Keep out of reach of children.

In case of overdose, get medical help or contact a Poison Control Center right away.

Directions

- drink a full glass of water with each dose
- adults and children 12 years of age and over: take 1 to 2 tablets every 4 hours while symptoms last
- do not take more than 12 tablets in 24 hours unless directed by a doctor
- children under 12 years of age: ask a doctor

Other information

- store at 25ºC (77ºF) excursions permitted between 15°-30°C (59°-86°F)
- see end flap for expiration date and lot number

Inactive ingredients

black iron oxide, cellulose, colloidal silicon dioxide, corn starch, D&C yellow #10 aluminum lake, FD&C yellow #6 aluminum lake, hypromellose, polydextrose, polyethylene glycol, polyvinyl acetate phthalate, propylene glycol, shellac wax, simethicone, sodium alginate, sodium bicarbonate, stearic acid, talc, titanium dioxide, triacetin, triethyl citrate

Questions?

1-800-255-5202 Ecotrin.com

PRINCIPAL DISPLAY PANEL

Ecotrin®
Safety Coated Aspirin
(NSAID) Pain Reliever
325 mg Regular Strength
125 Tablets

PRINCIPAL DISPLAY PANEL

Ecotrin®
Safety Coated Aspirin
(NSAID) Pain Reliever
325 mg Regular Strength
300 Tablets